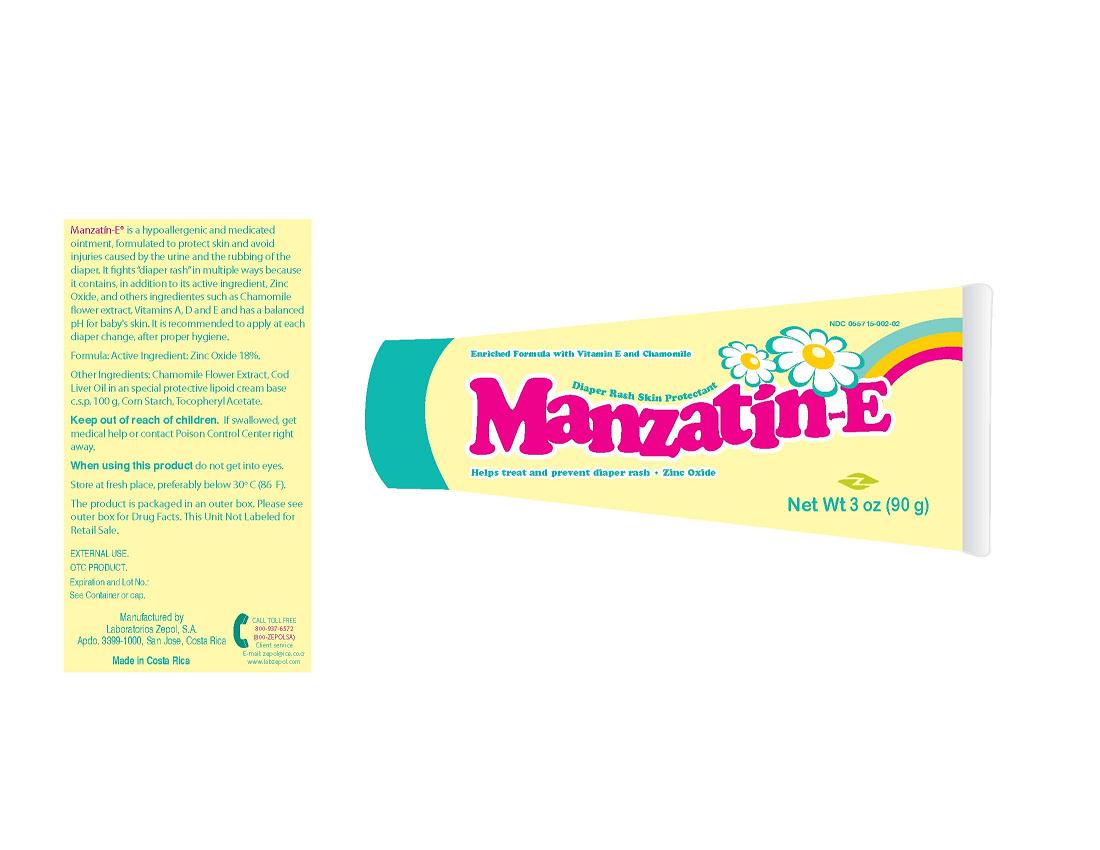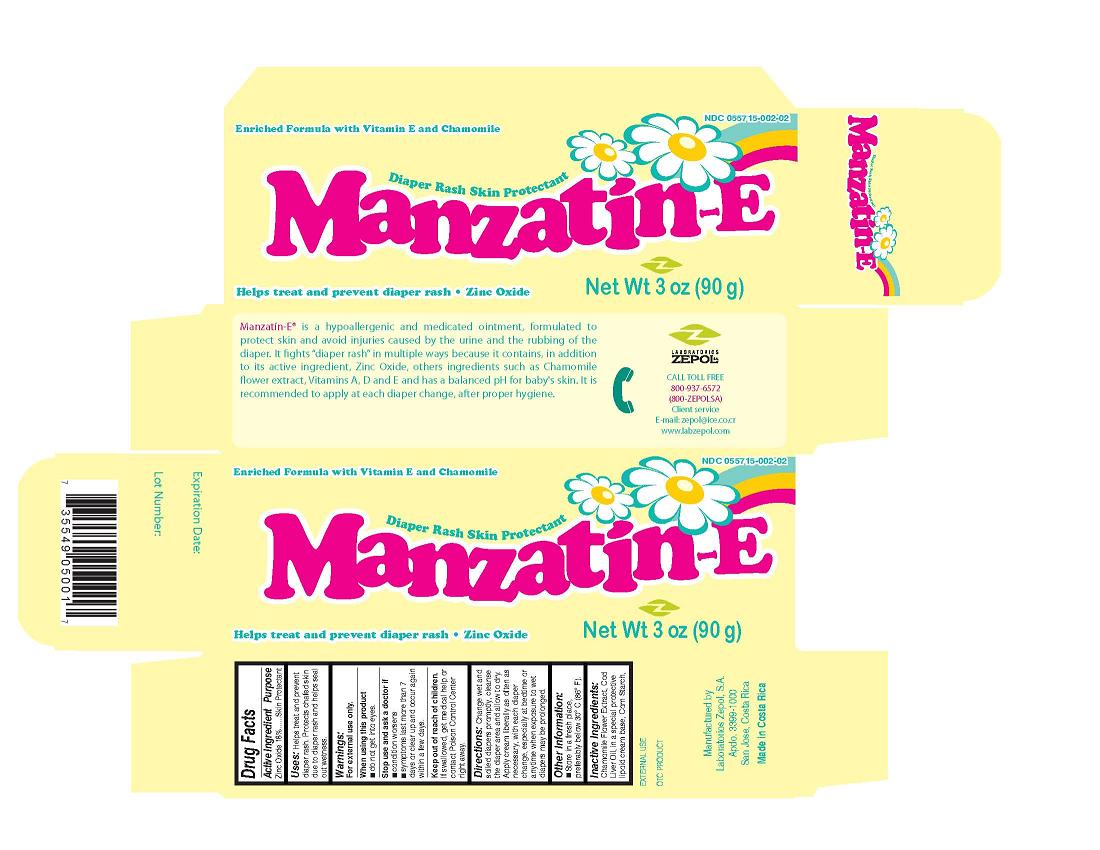 DRUG LABEL: Manzatin-E Diaper Rash Skin Protectant
NDC: 55715-002 | Form: OINTMENT
Manufacturer: Laboratorios Zepol S.A.
Category: otc | Type: HUMAN OTC DRUG LABEL
Date: 20231201

ACTIVE INGREDIENTS: ZINC OXIDE 18 g/100 g
INACTIVE INGREDIENTS: CHAMOMILE; COD LIVER OIL; STARCH, CORN

Manzatin-E Diaper Rash Skin Protectant

Active Ingredient

Zinc Oxide 18%

Purpose

Skin Protectant

Uses

Helps treat and prevent diaper rash. Protects chafed skin due to diaper rash and helps seal out wetness.

Warnings

For external use only.

When using this product

do not get into eyes

Stop using and ask a doctor if

-condition worsens
- symptoms last more than 7 days or clear up and occur again within a few days.

Keep out of reach of children

If swallowed, get medical help or contact a Poison Control Center right away.

Directions

Change wet and soiled diapers promptly, cleanse the diaper area and allow to dry. Apply cream liberally as often as necessary, with each diaper change, especially at bedtime or anytime when exposure to wet diapers may be prolonged.

Other Information

- Store in a fresh place,
preferably below 30 degrees C (86 degrees F).

Inactive Ingredients

Chamomile Flower Extract, CodmLiver Oil, in a special protective lipoid cream base, Corn Starch,